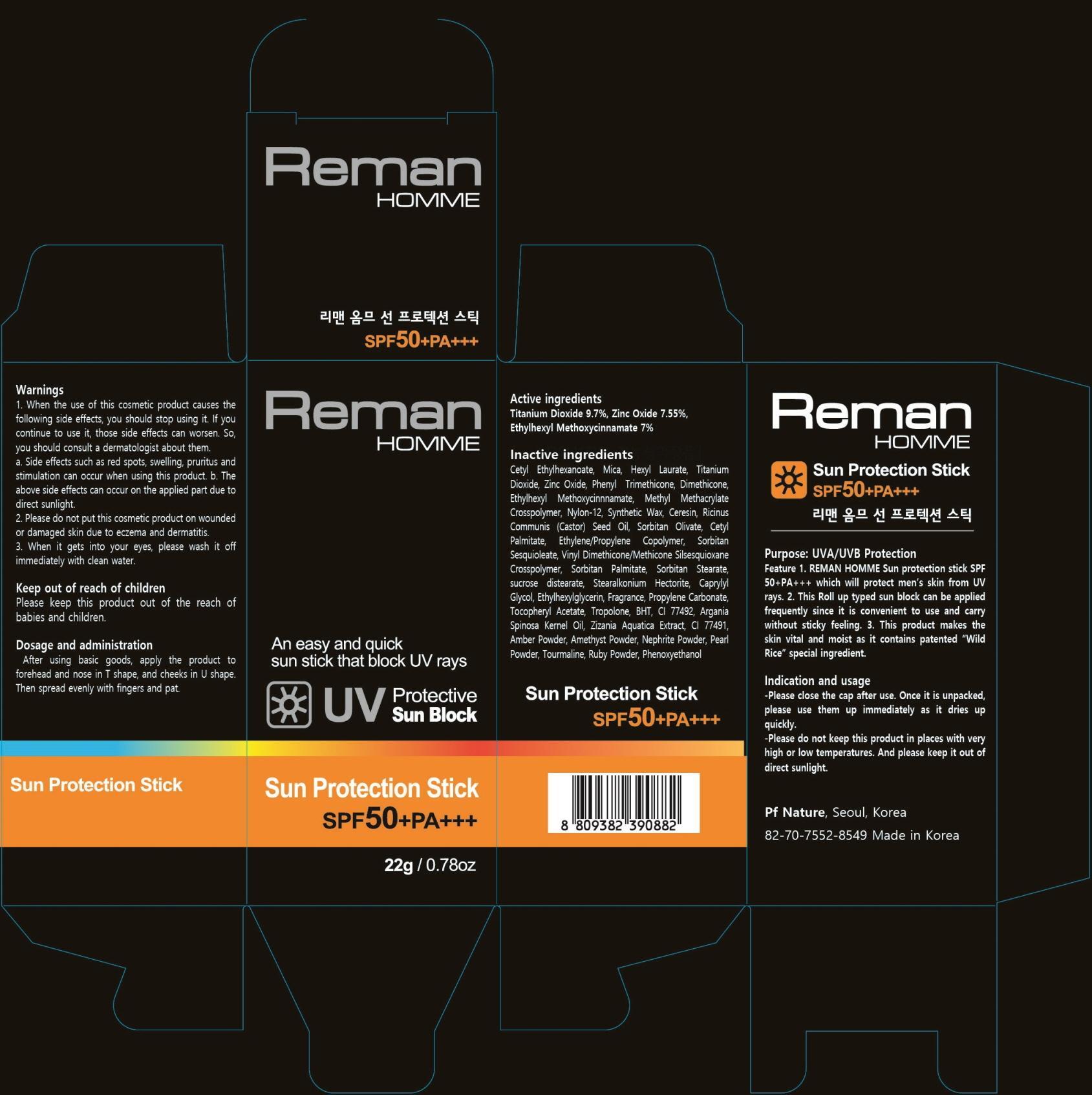 DRUG LABEL: REMAN HOMME SUN PROTECTION
NDC: 69226-010 | Form: STICK
Manufacturer: Pf Nature
Category: otc | Type: HUMAN OTC DRUG LABEL
Date: 20140930

ACTIVE INGREDIENTS: TITANIUM DIOXIDE 2.13 g/22 g; ZINC OXIDE 1.66 g/22 g; OCTINOXATE 1.54 g/22 g
INACTIVE INGREDIENTS: Mica; Dimethicone

ACTIVE INGREDIENT

Active ingredients: Titanium Dioxide 9.7%, Zinc Oxide 7.55%, Ethylhexyl Methoxycinnamate 7%

INACTIVE INGREDIENT

Inactive ingredients:
Cetyl Ethylhexanoate, Mica, Hexyl Laurate, Phenyl Trimethicone, Dimethicone, Methyl Methacrylate Crosspolymer, Nylon-12, Synthetic Wax, Ceresin, Ricinus Communis (Castor) Seed Oil, Sorbitan Olivate, Cetyl Palmitate, Ethylene/Propylene Copolymer, Sorbitan Sesquioleate,
Vinyl Dimethicone/Methicone Silsesquioxane Crosspolymer, Sorbitan Palmitate, Sorbitan Stearate, sucrose distearate, Stearalkonium Hectorite, Caprylyl Glycol, Ethylhexylglycerin, Fragrance, Propylene Carbonate, Tocopheryl Acetate, Tropolone, BHT, CI 77492, Argania Spinosa Kernel Oil, Zizania Aquatica Extract, CI 77491, Amber Powder, Amethyst Powder, Nephrite Powder, Pearl Powder, Tourmaline, Ruby Powder, Phenoxyethanol

PURPOSE

Purpose: UVA/UVB Protection

WARNINGS

1. When the use of this cosmetic product causes the following side effects, you should stop using it. If you continue to use it, those side effects can worsen. So, you should consult a dermatologist about them.
a. Side effects such as red spots, swelling, pruritus and stimulation can occur when using this product.
b. The above side effects can occur on the applied part due to direct sunlight.
2. Please do not put this cosmetic product on wounded or damaged skin due to eczema and dermatitis.
3. When it gets into your eyes, please wash it off immediately with clean water.

KEEP OUT OF REACH OF CHILDREN

Please keep this product out of the reach of babies and children.

INDICATIONS & USAGE

Indication and usage:
Please close the cap after use. Once it is unpacked, please use them up immediately as it dries up quickly.
Please do not keep this product in places with very high or low temperatures.
And please keep it out of direct sunlight.

DOSAGE & ADMINISTRATION

Dosage and administration:
After using basic goods, apply the product to forehead and nose in T shape, and cheeks in U shape. Then spread evenly with fingers and pat.